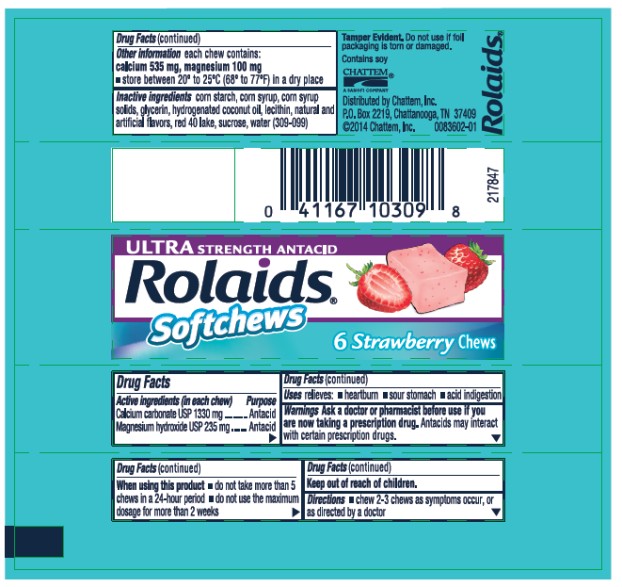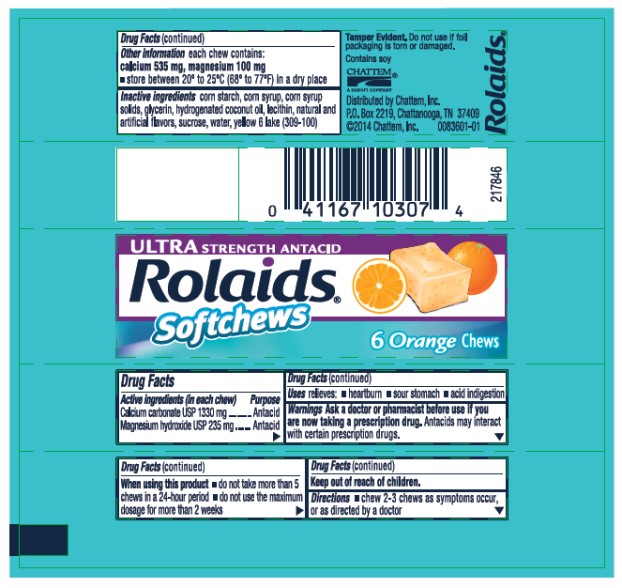 DRUG LABEL: Rolaids Ultra Strength Antacid Strawberry
NDC: 41167-1031 | Form: TABLET, CHEWABLE
Manufacturer: Chattem, Inc.
Category: otc | Type: HUMAN OTC DRUG LABEL
Date: 20260114

ACTIVE INGREDIENTS: CALCIUM CARBONATE 1330 mg/1 1; MAGNESIUM HYDROXIDE 235 mg/1 1
INACTIVE INGREDIENTS: STARCH, CORN; CORN SYRUP; GLYCERIN; HYDROGENATED COCONUT OIL; EGG PHOSPHOLIPIDS; FD&C RED NO. 40; SUCROSE; WATER

Rolaids Ultra Strength Antacid Softchews

ULTRA STRENGTH ANTACID Rolaids Softchews- Strawberry

Drug Facts

Active ingredients

(in each chew)
Calcium carbonate USP 1330 mg
Magnesium hydroxide USP 235 mg

Purpose

Antacid
Antacid

Use

relieves:

- heartburn
- sour stomach
- acid indigestion

Warnings

Ask a doctor or pharmacist before use if you are

now taking a prescription drug. Antacids may interact with certain prescription drugs.

When using this product

- do not take more than 5 chews in a 24-hour period
- do not use the maximum dosage for more than 2 weeks

Directions

- chew 2-3 chews as symptoms occur, or as directed by a doctor

Other information

each tablet contains: calcium 535 mg, magnesium 100 mg

Inactive ingredients

corn starch, corn syrup, corn syrup solids, glycerin, hydrogenated coconut oil, lecithin, natural and artificial flavors, red 40 lake, sucrose, water (309-099)

ULTRA STRENGTH ANTACID Rolaids Softchews- Orange

Drug Facts

Active ingredients

(in each chew)
Calcium carbonate USP 1330 mg
Magnesium hydroxide USP 235 mg

Purpose

Antacid
Antacid

Use

relieves:

- heartburn
- sour stomach
- acid indigestion

Warnings

Ask a doctor or pharmacist before use if you are

now taking a prescription drug. Antacids may interact with certain prescription drugs.

When using this product

- do not take more than 5 chews in a 24-hour period
- do not use the maximum dosage for more than 2 weeks

Directions

- chew 2-3 chews as symptoms occur, or as directed by a doctor

Other information

each tablet contains: calcium 535 mg, magnesium 100 mg

Inactive ingredients

corn starch, corn syrup, corn syrup solids, glycerin, hydrogenated coconut oil, lecithin, natural and artificial flavors, sucrose, water. yellow 6 lake (309-100)

PRINCIPAL DISPLAY PANEL

ULTRA STRENGTH ANTACID
Rolaids®
Softchews
6 Strawberry Chews

PRINCIPAL DISPLAY PANEL

ULTRA STRENGTH ANTACID
Rolaids®
Softchews
6 Orange Chews